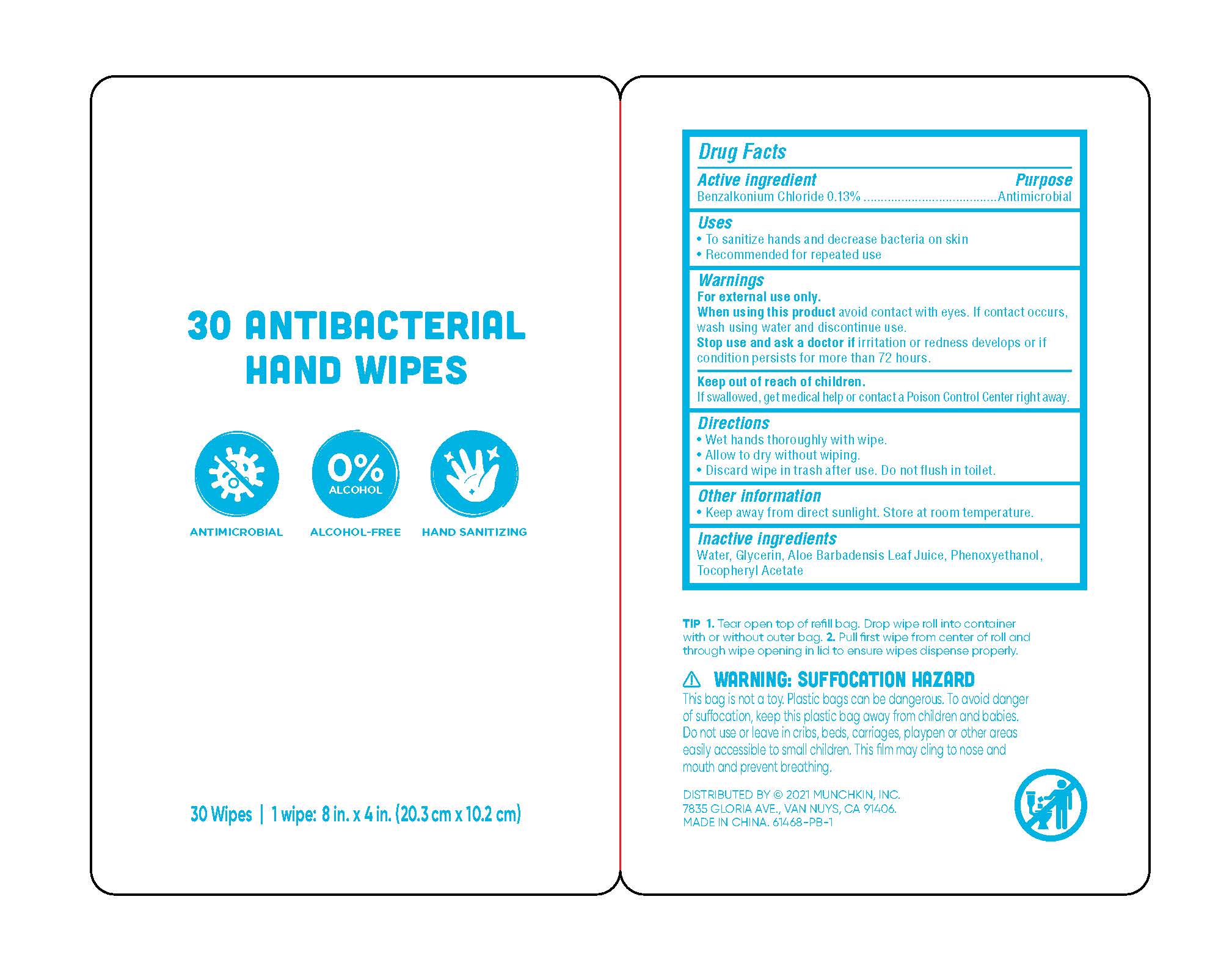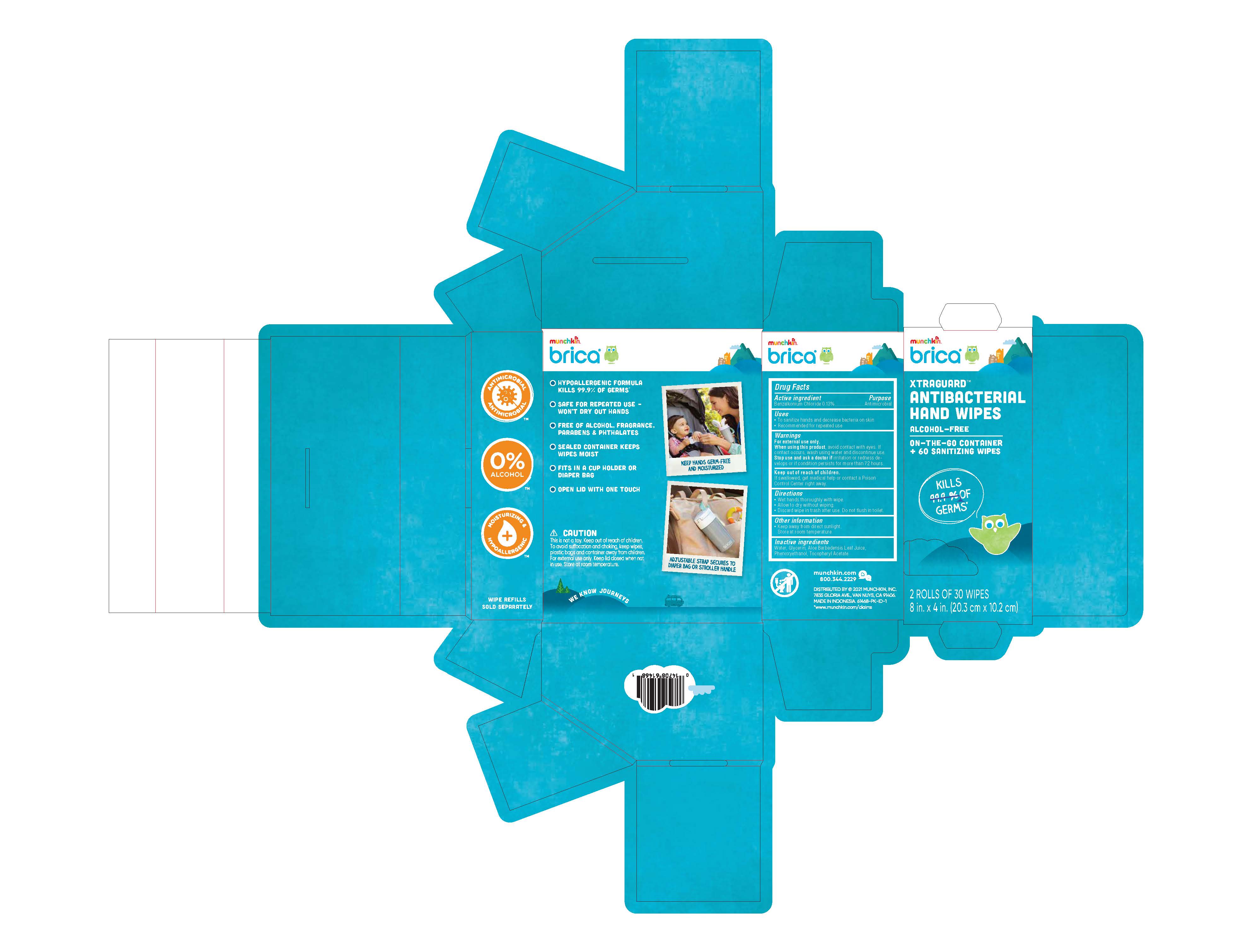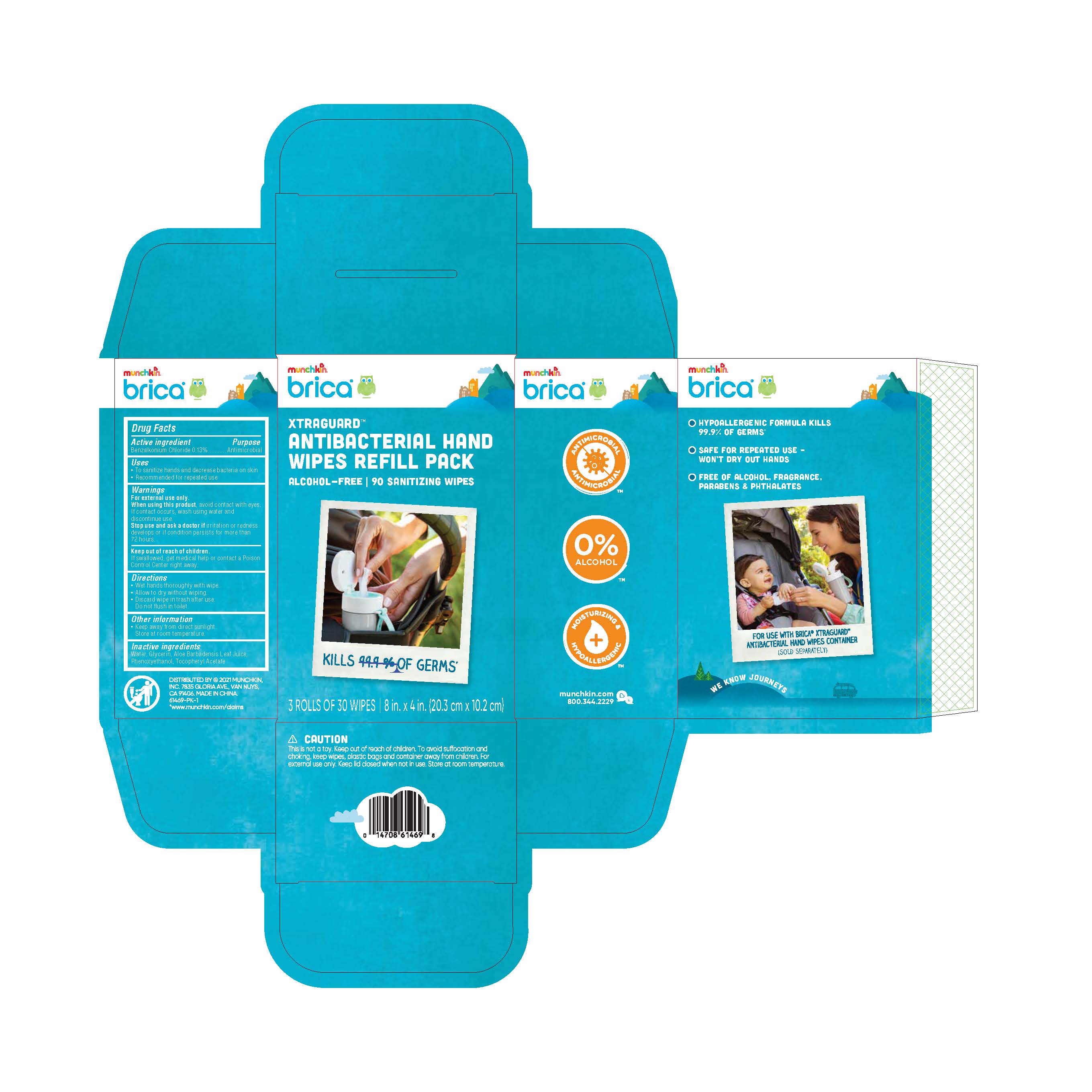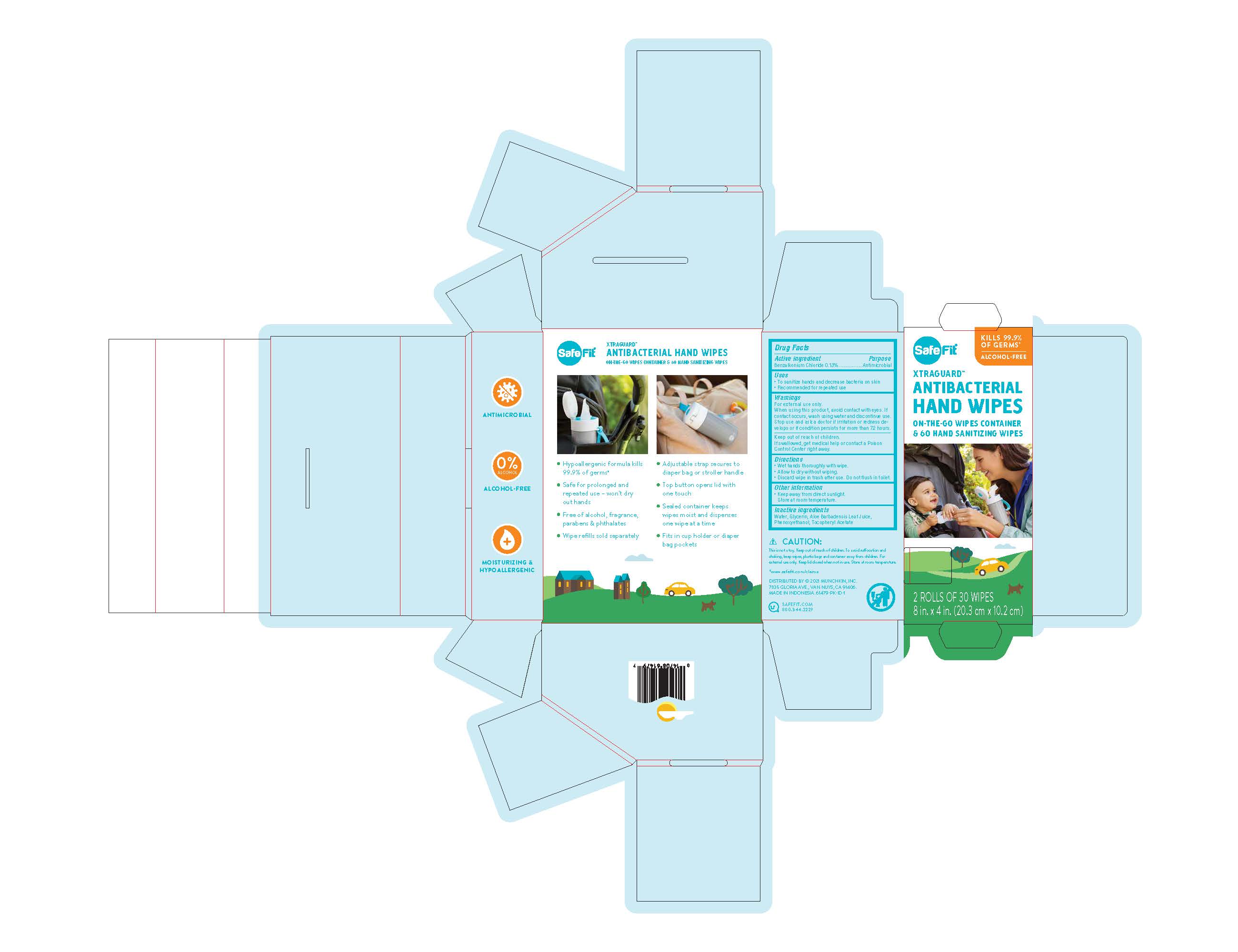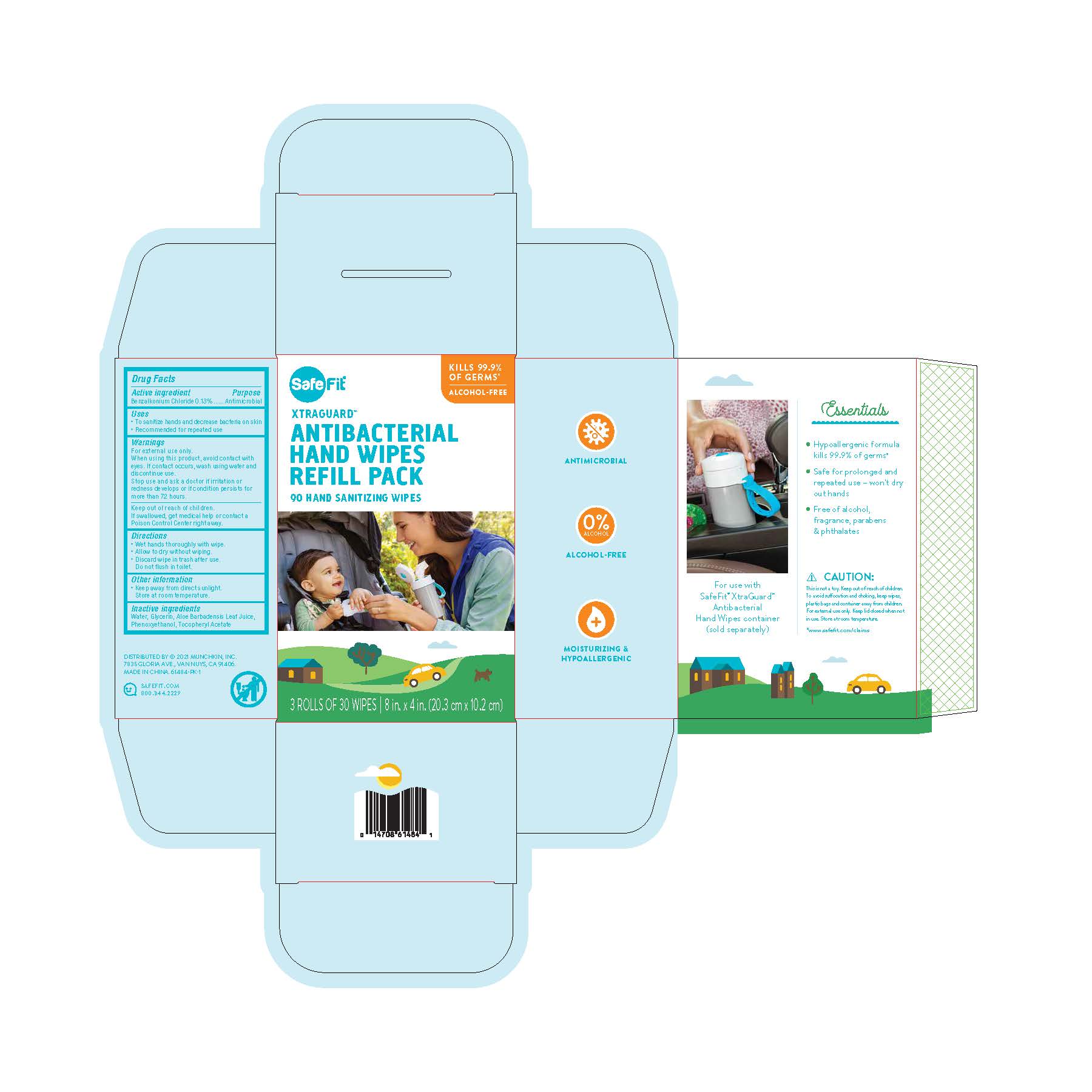 DRUG LABEL: Xtraguard Antibacterial Hand Wipes
NDC: 81725-614 | Form: SWAB
Manufacturer: Munchkin Inc.
Category: otc | Type: HUMAN OTC DRUG LABEL
Date: 20210512

ACTIVE INGREDIENTS: BENZALKONIUM CHLORIDE 0.13 g/100 g
INACTIVE INGREDIENTS: PHENOXYETHANOL 0.3 g/100 g; ALOE VERA LEAF 0.2 g/100 g; WATER 98.27 g/100 g; GLYCERIN 1 g/100 g; .ALPHA.-TOCOPHEROL ACETATE, D- 0.1 g/100 g

DOSAGE AND ADMINISTRATION

30 Wipes | 1 wipe: 8 in. x 4 in. (20.3 cm x 10.2 cm)

ACTIVE INGREDIENT

Benzalkonium Chloride 0.13% - Antimicrobial

PURPOSE

Antimicrobial

Uses

- To sanitize hands and decrease bacteria on skin
- Recommended for repeated use

Warnings

For external use only.

When using this product avoid contact with eyes. If contact occurs, wash using water and discontinue use.

Stop use and ask a doctor if irritation or redness develops or if condition persists for more than 72 hours.

Keep out of reach of children.

If swallowed, get medical help or contact a Poison Control Center right away.

Directions

- Wet hands thoroughly with wipe.
- Allow to dry without wiping.
- Discard wipe in trash after use. Do not flush in toilet.

Other information

- Keep away from direct sunlight. Store at room temperature.

Inactive ingredients

Water, Glycerin, Aloe Barbadensis Leaf Juice, Phenoxyethanol, Tocopheryl Acetate

PACKAGE LABEL

30 Wipes | NDC: 81725-614-01

PACKAGE LABEL

60 Wipes | NDC: 81725-614-10

PACKAGE LABEL

60 Wipes | NDC: 81725-614-20

PACKAGE LABEL

90 Wipes | NDC: 81725-614-15

PACKAGE LABEL

90 Wikpes | NDC: 81725-614-25